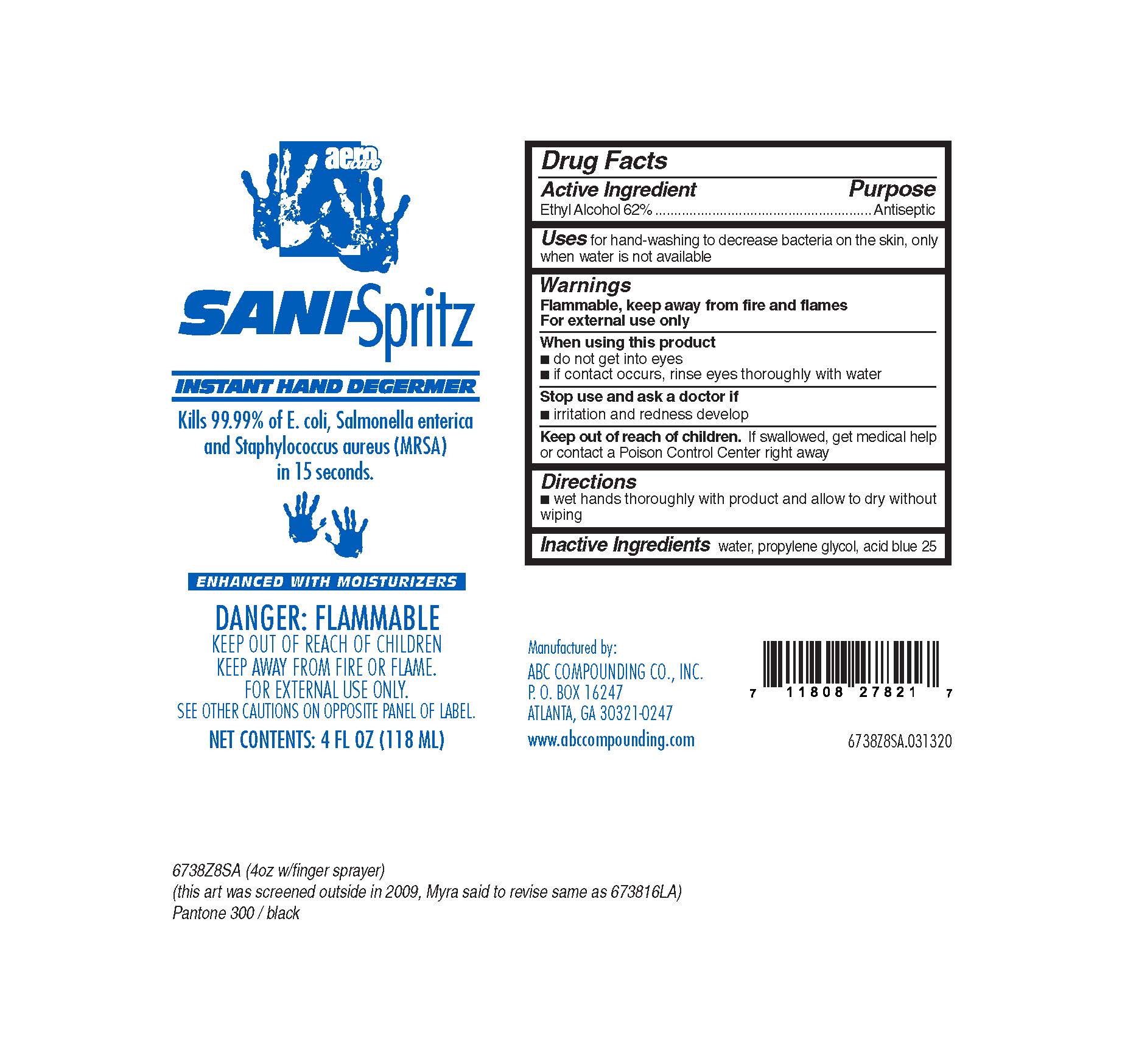 DRUG LABEL: Sani-Spritz
NDC: 62257-738 | Form: LIQUID
Manufacturer: ABC Compounding Co., Inc.
Category: otc | Type: HUMAN OTC DRUG LABEL
Date: 20251119

ACTIVE INGREDIENTS: ALCOHOL 0.7 mL/1 mL
INACTIVE INGREDIENTS: WATER; PROPYLENE GLYCOL

Sani-Spritz 6738 Drug Facts and Label

Drug Facts Box OTC-Active Ingredient Section

Ethyl Alcohol 62%

Drug Facts Box OTC-Purpose Section

Antiseptic

Drug Facts Box OTC-Indications & Usage Section

for hand-washing to decrease bacteria on the skin, only when water is not available

Drug Facts Box OTC-Warnings Section

FLAMMABLE, keep away from fire and flames

For external use only

Drug Facts Box OTC-When Using Section

do not get into eyes

if contact occurs, rinse eyes thoroughly with water

Drug Facts Box OTC-Stop Use Section

irritation and redness develop

Drug Facts Box OTC-Keep Out of Reach of Children Section

if swallowed, get medical help or contact a Poison Control Center right away

Drug Facts Box OTC-Dosage & Administration Section

press pump twice to deliver two squirts (about a quarter size) of foaming product onto the palm of your hand

rub hands together and allow to dry without wiping

Drug Facts Box OTC-Inactive Ingredient Section

water, propylene glycol, acid blue 25

Sani-Spritz

Sani-Spirtz Label